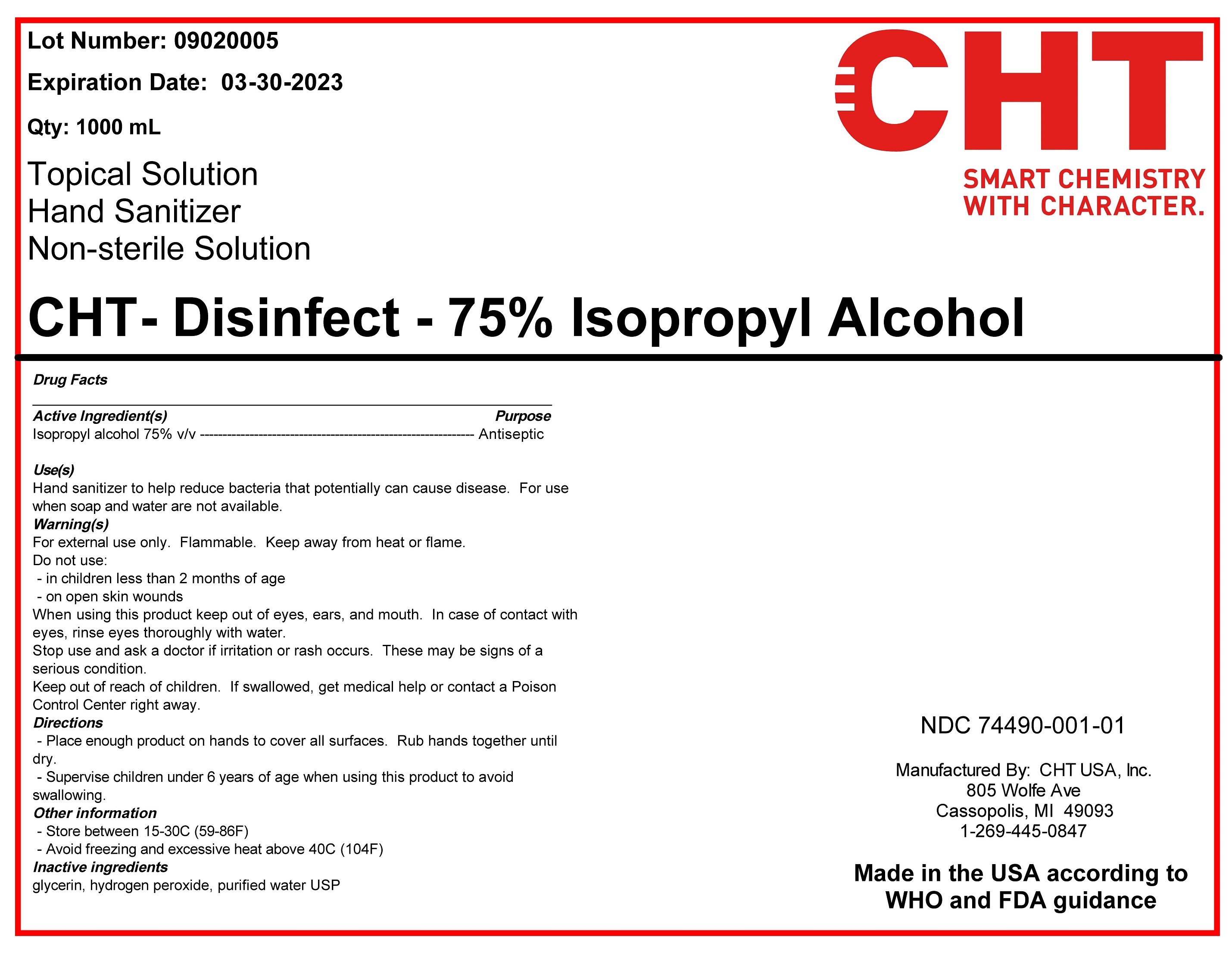 DRUG LABEL: CHT Disinfect - Isopropyl Alcohol 75%
NDC: 74490-001 | Form: SOLUTION
Manufacturer: CHT USA Inc
Category: otc | Type: HUMAN OTC DRUG LABEL
Date: 20201204

ACTIVE INGREDIENTS: ISOPROPYL ALCOHOL 75 L/100 L
INACTIVE INGREDIENTS: GLYCERIN 1.45 L/100 L; HYDROGEN PEROXIDE 0.125 L/100 L; WATER 18.425 L/100 L

Drug Facts
__________________________________________________________________
Active Ingredient(s) Purpose
Isopropyl alcohol 75% v/v ------------------------------------------------------------- Antiseptic
Use(s)
Hand sanitizer to help reduce bacteria that potentially can cause disease. For use
when soap and water are not available.
Warning(s)
For external use only. Flammable. Keep away from heat or flame.
Do not use:
- in children less than 2 months of age
- on open skin wounds
When using this product keep out of eyes, ears, and mouth. In case of contact with
eyes, rinse eyes thoroughly with water.
Stop use and ask a doctor if irritation or rash occurs. These may be signs of a
serious condition.
Keep out of reach of children. If swallowed, get medical help or contact a Poison
Control Center right away.
Directions
- Place enough product on hands to cover all surfaces. Rub hands together until
dry.
- Supervise children under 6 years of age when using this product to avoid
swallowing.
Other information
- Store between 15-30C (59-86F)
- Avoid freezing and excessive heat above 40C (104F)
Inactive ingredients
glycerin, hydrogen peroxide, purified water USP

Active Ingredient(s)

Isopropyl Alcohol 75% v/v. Purpose: Antiseptic

Purpose

Antiseptic, Hand Sanitizer

Use

Hand Sanitizer to help reduce bacteria that potentially can cause disease. For use when soap and water are not available.

Warnings

For external use only. Flammable. Keep away from heat or flame

Do not use

- in children less than 2 months of age
- on open skin wounds

When using this product keep out of eyes, ears, and mouth. In case of contact with eyes, rinse eyes thoroughly with water.
Stop use and ask a doctor if irritation or rash occurs. These may be signs of a serious condition.
Keep out of reach of children. If swallowed, get medical help or contact a Poison Control Center right away.

Stop use and ask a doctor if irritation or rash occurs. These may be signs of a serious condition.

Keep out of reach of children. If swallowed, get medical help or contact a Poison Control Center right away.

Directions

- Place enough product on hands to cover all surfaces. Rub hands together until dry.
- Supervise children under 6 years of age when using this product to avoid swallowing.

Other information

- Store between 15-30C (59-86F)
- Avoid freezing and excessive heat above 40C (104F)

Inactive ingredients

glycerin, hydrogen peroxide, purified water USP

Package Label - Principal Display Panel

1 L (1000 mL) NDC: 74490-001-01